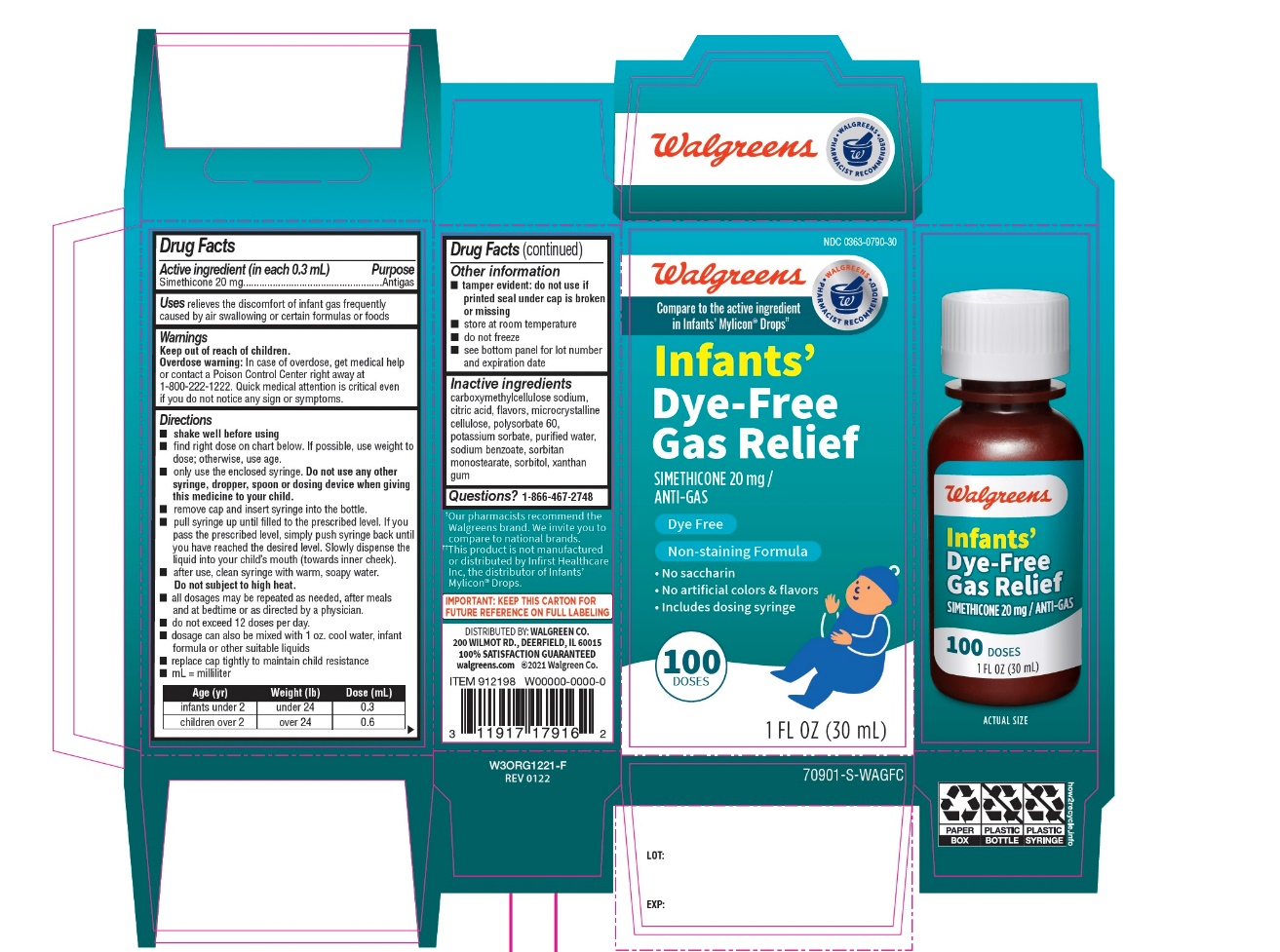 DRUG LABEL: Walgreens Infants Dye Free Gas Relief
NDC: 0363-0790 | Form: EMULSION
Manufacturer: WALGREEN CO.
Category: otc | Type: HUMAN OTC DRUG LABEL
Date: 20251202

ACTIVE INGREDIENTS: DIMETHICONE, UNSPECIFIED 20 mg/0.3 mL
INACTIVE INGREDIENTS: CARBOXYMETHYLCELLULOSE SODIUM, UNSPECIFIED; ANHYDROUS CITRIC ACID; MICROCRYSTALLINE CELLULOSE; POLYSORBATE 60; POTASSIUM SORBATE; WATER; SODIUM BENZOATE; SORBITAN MONOSTEARATE; SORBITOL; XANTHAN GUM

Walgreens infants’ Dye- Free Gas Relief Simethicone 20 mg per Dose /Anti-Gas

Active ingredient (in each 0.3 mL)

Simethicone 20 mg

Purpose

Antigas

Uses

relieves the discomfort of infant gas frequently caused by air swallowing or certain formulas or foods

Directions

- shake well before using
- find right dose on chart below. if possible, use weight to dose; otherwise use age.
- only use the enclosed syringe. Do not use other syringe, dropper, spoon or dosing device when giving this medicine to your child.
- remove cap and insert syringe into the bottle.
- pull syringe up until filled to the prescribed level, if you pass the prescribed level, simply push syringe back until you have reached the desired level, Slowly dispense the liquid into your child’s mouth (towards inner cheek)
- all dosages may be repeated needed, after meals and at bedtime or as directed by a physician.
- do not exceed 12 doses per day.
- dosage can also be mixed with 1 oz. cool water, infant formula or other suitable liquids
- replace cap tightly to maintain child resistance
- mL= milliliter

Age (yr) | Weight (lb) | Dose(mL)
infants under 2 | under 24 | 0.3
children over 2 | over 24 | 0.6

Other information

- tamper evident: do not use if printed seal under cap is broken or missing
- store at room temperature
- do not freeze
- see bottom panel for lot number and expiration date

Inactive ingredients

carboxymethylcellulose sodium, citric acid, microcrystalline cellulose, natural flavors, polysorbate 60, potassium sorbate, purified water, sodium benzoate, sorbitan monostearate, sorbitol, xanthan gum.

Questions?

1-866-467-2748

Principal Display Panel

Walgreens

Compare to infant’s Mylicon Gas Relief active ingredient††

Infants'

Dye- Free

Gas Relief

Simethicone 20 mg PER DOSE /ANTI-GAS

- DYE FREE
- NONSTAINING FORMULA
- ALCOHOL FREE

- No saccharin
- No artificial flavor
- Includes dosing syringe

100 DOSES DYE FREE

1 FL OZ (30 mL)

200 WILMOT RD., DEERFIELD, IL 60015

100% SATISFACTION GUARANTEED

Walgreens.com ©2017 Walgreen Co,

WALGREENS PHARMACIST RECOMMENDED‡

‡Walgreens Pharmacist Survey

‡‡ This product is not manufactured or distributed by infirst Healthcare Inc., the distributor of Infants’ Mylicon®Gas Relief.

- IMPORTANT: KEEP THIS CARTON FOR FUTURE REFERENCE ON FULL LABELING